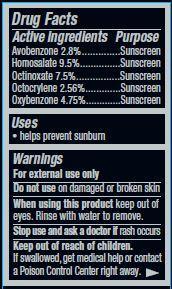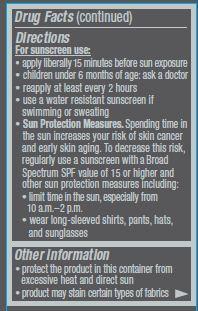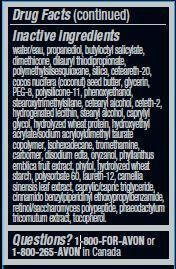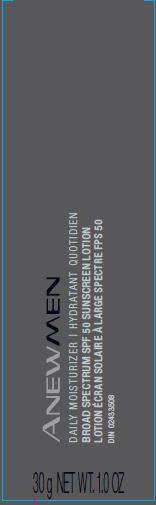 DRUG LABEL: Anew Men
NDC: 10096-0326 | Form: LOTION
Manufacturer: New Avon LLC
Category: otc | Type: HUMAN OTC DRUG LABEL
Date: 20160301

ACTIVE INGREDIENTS: AVOBENZONE 28 mg/1 g; HOMOSALATE 95 mg/1 g; OCTINOXATE 75 mg/1 g; OCTOCRYLENE 25.6 mg/1 g; OXYBENZONE 47.5 mg/1 g

Active ingredients
Avobenzone 2.8%...........................
Homosalate 9.5%...........................
Octinoxate 7.5%............................
Octocrylene 2.56%.......................
Oxybenzone 4.75%........................

Purpose
.................Sunscreen
.................Sunscreen
................Sunscreen
................Sunscreen
..............Sunscreen

Uses
• helps prevent sunburn

Warnings
For external use only

Do not use on damaged or broken skin

When using this product keep out of eyes. Rinse with water to remove.

Stop use and ask a doctor if rash occurs

Keep out of reach of children. If swallowed, get medical help or contact a Poison Control Center right away.

Directions

For sunscreen use:
• apply liberally 15 minutes before sun exposure
• children under 6 months of age: ask a doctor
• reapply at least every 2 hours
• use a water resistant sunscreen if swimming or sweating
• Sun Protection Measures. Spending time in the sun increases your risk of skin cancer and early skin aging. To decrease this risk, regularly
use a sunscreen with a Broad Spectrum SPF value of 15 or higher and other sun protection measures including:
• limit time in the sun, especially from 10 a.m. – 2 p.m.
• wear long-sleeved shirts, pants, hats, and sunglasses

Inactive ingredients
water/eau, propanediol, butyloctyl salicylate, dimethicone, dilauryl thiodipropionate, polymethylsilsesquioxane, silica, ceteareth-20,cocos nucifera (coconut) seed butter, glycerin, PEG-8, polysilicone-11, phenoxyethanol, stearoxytrimethylsilane, cetearyl alcohol, ceteth-2, hydrogenated lecithin, stearyl alcohol, caprylyl glycol, hydrolyzed wheat protein, hydroxyethyl acrylate/sodium acryloyldimethyl taurate
copolymer, isohexadecane, tromethamine, carbomer, disodium edta, oryzanol, phyllanthus emblica fruit extract, phytol, hydrolyzed wheat
starch, polysorbate 60, laureth-12, camellia sinensis leaf extract, caprylic/capric triglyceride, cinnamido benzylpiperidinyl ethoxypropylbenzamide, retinol/saccharomyces polypeptide, phaeodactylum tricornutum extract, tocopherol.

Questions?
1-800-FOR-AVON or 1-800-265-AVON in Canada